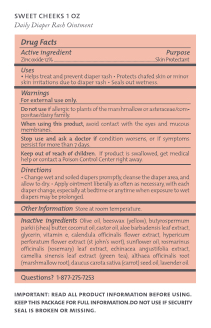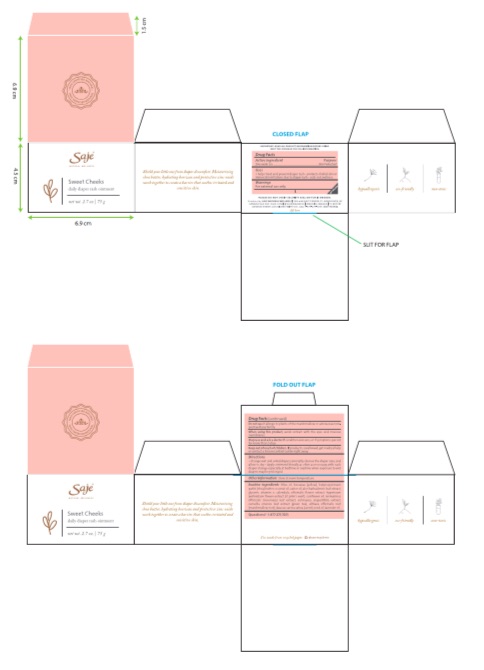 DRUG LABEL: Sweet cheeks
NDC: 70983-021 | Form: OINTMENT
Manufacturer: Saje Natural Business Inc.
Category: otc | Type: HUMAN OTC DRUG LABEL
Date: 20260113

ACTIVE INGREDIENTS: ZINC OXIDE 9 g/75 g
INACTIVE INGREDIENTS: SHEA BUTTER; COCONUT OIL; YELLOW WAX; CASTOR OIL; SUNFLOWER OIL; TOCOPHEROL; HYPERICUM PERFORATUM FLOWER; LAVENDER OIL; ALOE VERA LEAF; GLYCERIN; OLIVE OIL; CALENDULA OFFICINALIS FLOWER; ROSEMARY; ECHINACEA ANGUSTIFOLIA; GREEN TEA LEAF; ALTHAEA OFFICINALIS ROOT; CARROT SEED OIL

Sweet cheeks

Active ingredient

Zinc Oxide 12%

Purpose

Skin protectant

Uses

helps treat and prevent diaper rash. protects chafed skin or minor skin irritations due to diaper rash. seals out wetness.

Warnings

Warnings

-Stop use and ask a doctor if condition worsens, or if symptoms persist for more than 7 days.

Warnings

-Do not use if allergic to plants of the marshmallow or asteraceae/compositae/daisy family.

Warnings

-When using this product, avoid contact with the eyes and mucous membranes.

Warnings

-Keep out of reach of children. If product is swallowed, get medical help or contact a Poison Control Center right away.

Directions

-Change wet and soiled diapers promptly, cleanse the diaper area, and allow to dry.

-Apply ointment liberally as often as necessary, with each diaper change, especially at bedtime or anytime when exposure to wet diapers may be prolonged.

Other information

-Store at room temperature.

Inactive ingredients

Olive oil, beeswax (yellow), butyrospermum parkii (shea) butter, coconut oil, castor oil, aloe barbadensis leaf extract, glycerin, vitamin e, calendula officinalis flower extract, hypericum perforatum flower extract (st john's wort), sunflower oil, rosmarinus officinalis (rosemary) leaf extract, echinacea angustifolia extract, camellia sinensis leaf extract (green tea), althaea officinalis root (marshmallow root), daucus carota sativa (carrot) seed oil, lavender oil

Questions?

1-877-275-7253

Principal display panel information

daily diaper rash ointment
net wt. 75g (2.7 oz) and net wt. 30g (1oz)
daily diaper rash ointment